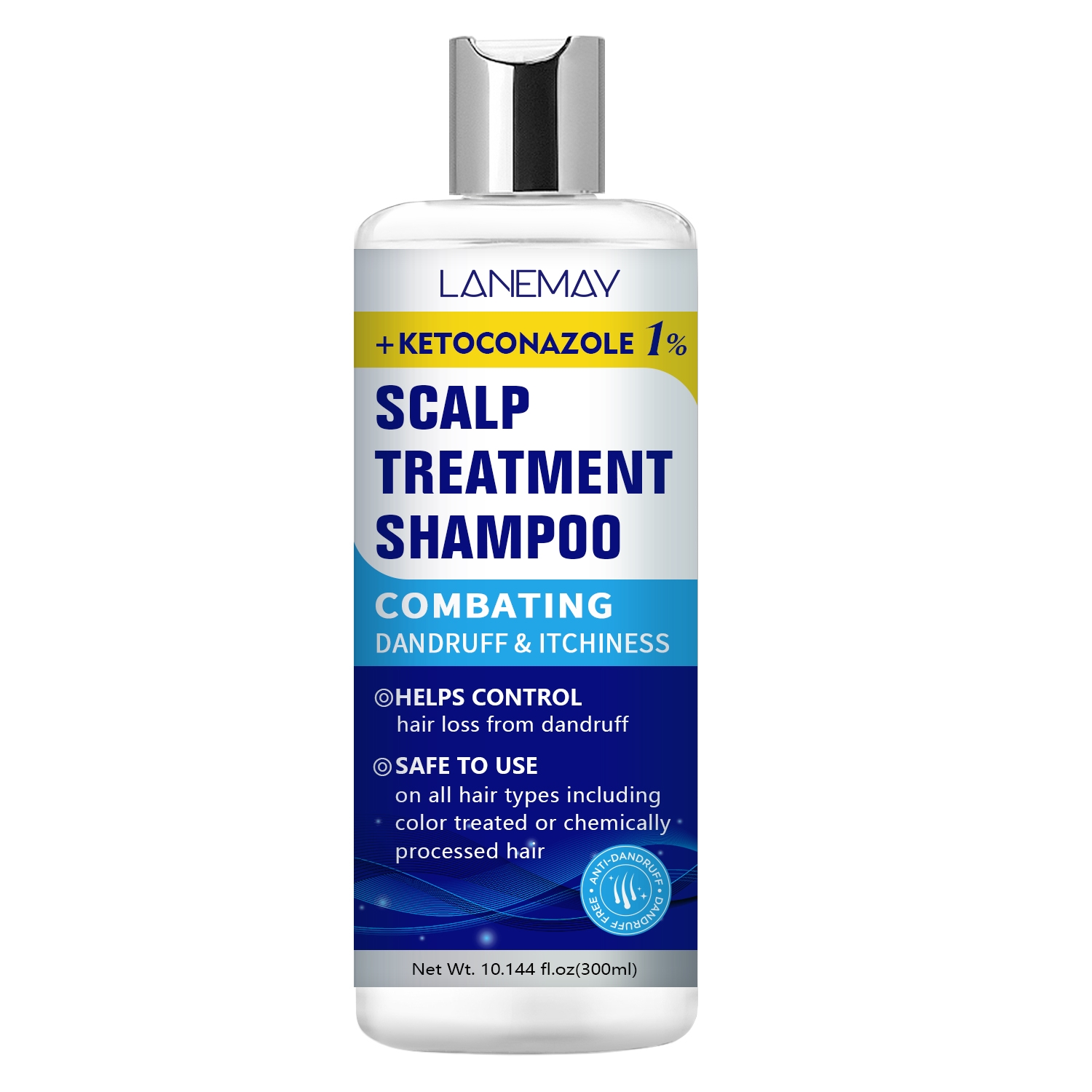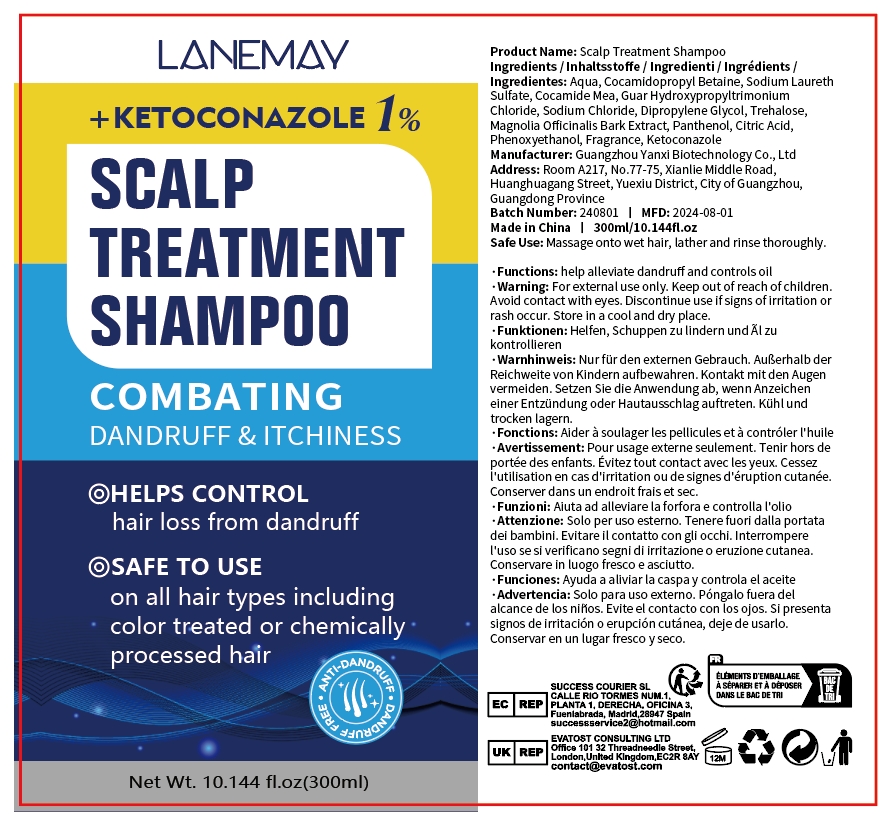 DRUG LABEL: Scalp TreatmentShampoo
NDC: 84025-232 | Form: LIQUID
Manufacturer: Guangzhou Yanxi Biotechnology Co., Ltd
Category: otc | Type: HUMAN OTC DRUG LABEL
Date: 20241023

ACTIVE INGREDIENTS: COCAMIDE MEA 15 mg/300 mL; PANTHENOL 13 mg/300 mL
INACTIVE INGREDIENTS: WATER

DOSAGE AND ADMINISTRATION

Massage onto wet hair, lather and rinse thoroughly.

WARNINGS

Keep out of children

INACTIVE INGREDIENT

Aqua

INDICATIONS AND USAGE

For daily hair care

Keep out of children

PURPOSE

Help control hair loss from dandruff